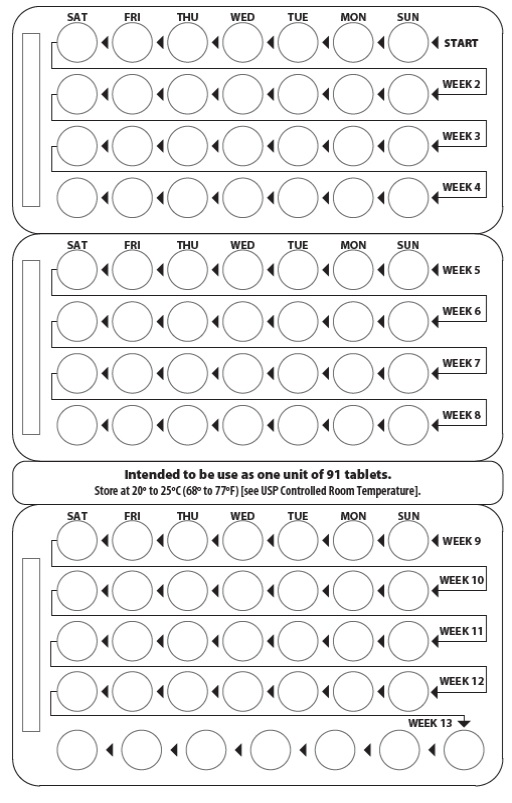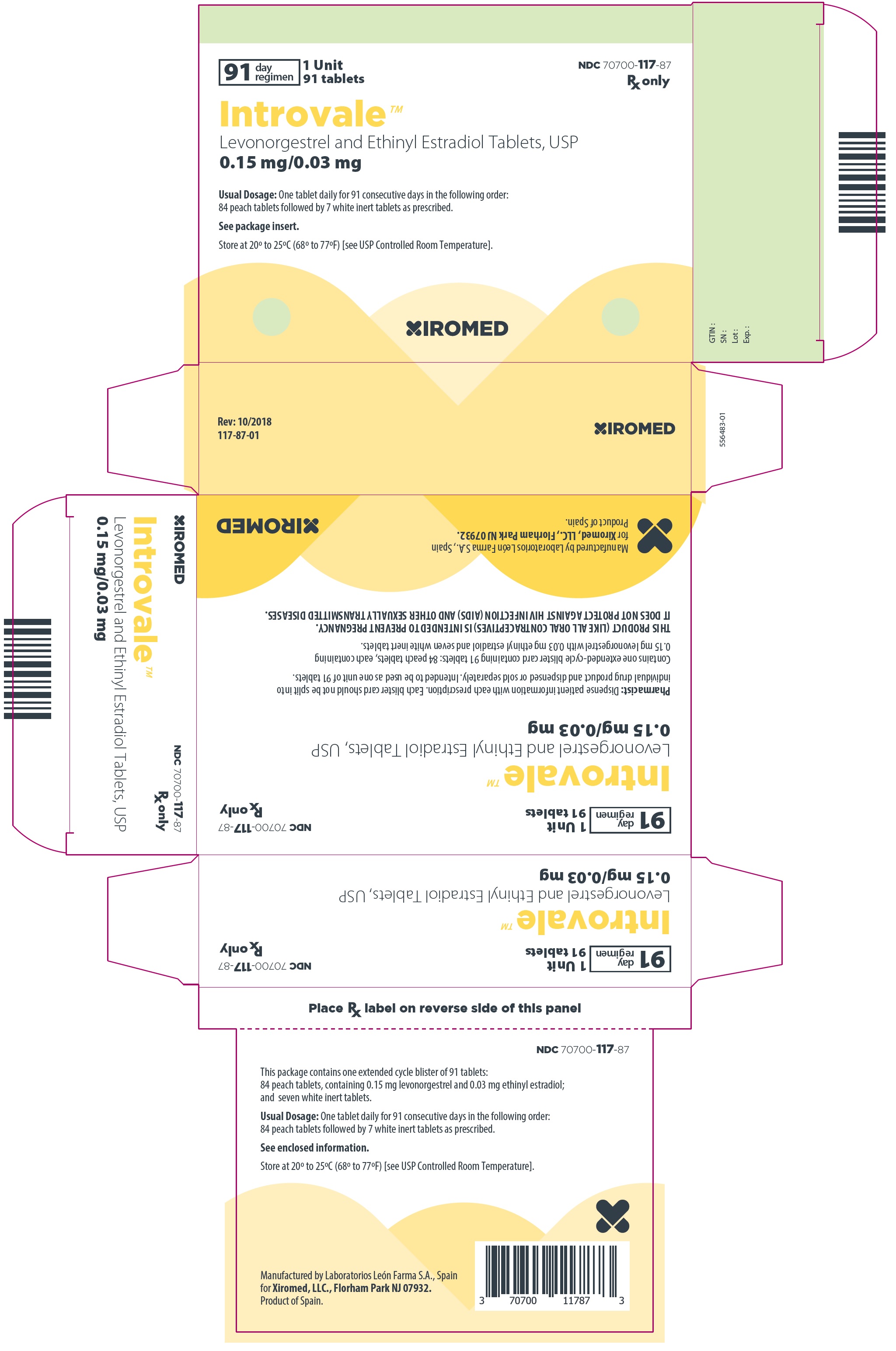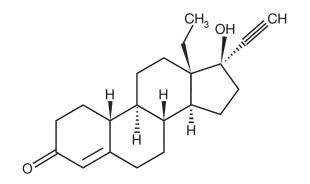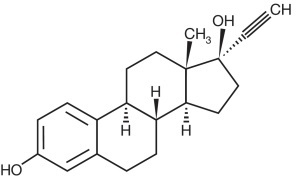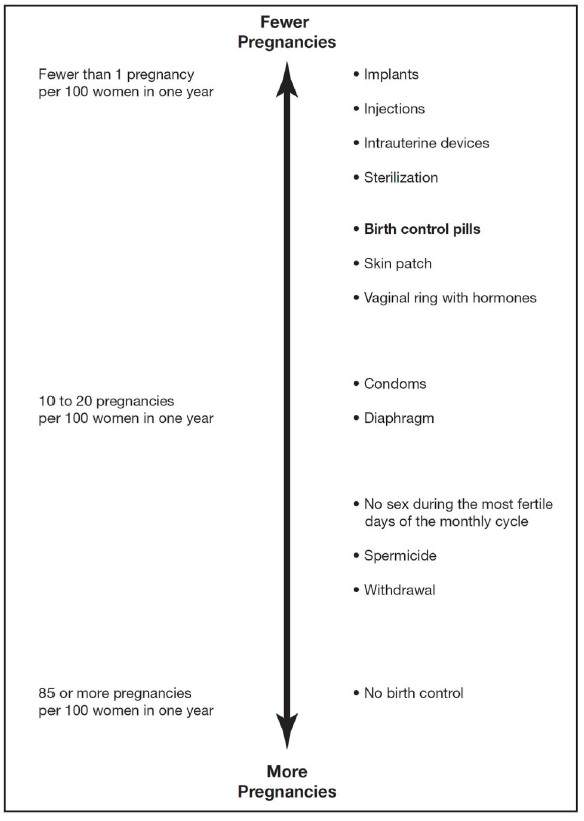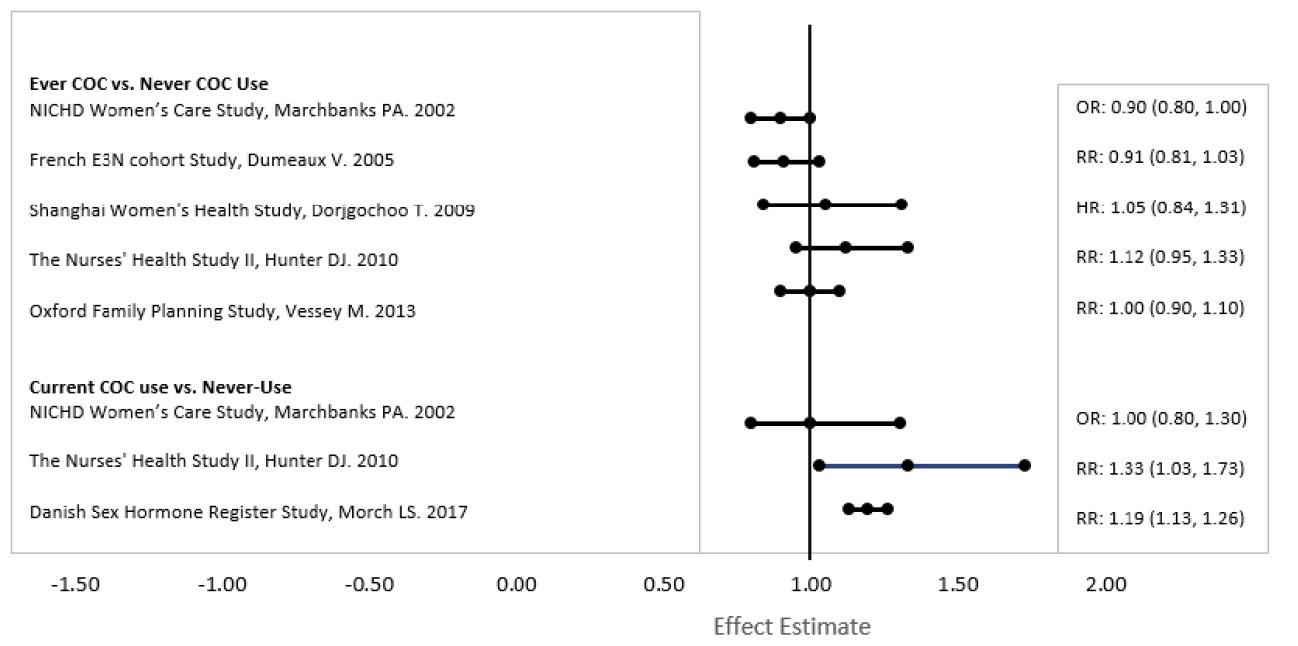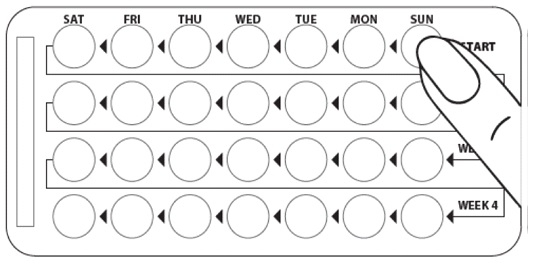 DRUG LABEL: Introvale
NDC: 70700-117 | Form: KIT | Route: ORAL
Manufacturer: Xiromed, LLC.
Category: prescription | Type: HUMAN PRESCRIPTION DRUG LABEL
Date: 20220609

ACTIVE INGREDIENTS: LEVONORGESTREL 0.15 mg/1 1; ETHINYL ESTRADIOL 0.03 mg/1 1
INACTIVE INGREDIENTS: MAGNESIUM STEARATE; POVIDONE, UNSPECIFIED; POLYVINYL ALCOHOL; POLYETHYLENE GLYCOL, UNSPECIFIED; TITANIUM DIOXIDE; TALC; FERRIC OXIDE YELLOW; FERRIC OXIDE RED; FERROSOFERRIC OXIDE; ANHYDROUS LACTOSE; ANHYDROUS LACTOSE; MAGNESIUM STEARATE; POVIDONE, UNSPECIFIED; POLYVINYL ALCOHOL; POLYETHYLENE GLYCOL, UNSPECIFIED; TALC; TITANIUM DIOXIDE

HIGHLIGHTS OF PRESCRIBING INFORMATION

These highlights do not include all the information needed to use INTROVALE safely and effectively. See full prescribing information for INTROVALE.
Introvale®
Levonorgestrel and Ethinyl Estradiol Tablets, USP
0.15 mg/0.03 mg
for oral use
Initial U.S. Approval: 1982

WARNING: CIGARETTE SMOKING AND SERIOUS CARDIOVASCULAR EVENTS

See full prescribing information for complete boxed warning.

- Introvale (levonorgestrel and ethinyl estradiol tablets) is contraindicated in women over 35 years old who smoke. (4)
- Cigarette smoking increases the risk of serious cardiovascular events from combination oral contraceptive (COC) use. (4)

RECENT MAJOR CHANGES

Warnings and Precautions, Malignant Neoplasms (5.11) 04/2022

1 INDICATIONS AND USAGE

Introvale is an estrogen/progestin COC indicated for use by women to prevent pregnancy. (1)

2 DOSAGE AND ADMINISTRATION

- Take one tablet daily by mouth at the same time every day for 91 days. (2.1)
- Take tablets in the order directed on the Extended-Cycle Blister Cards. (2.2)

3 DOSAGE FORMS AND STRENGTHS

Introvale (levonorgestrel and ethinyl estradiol tablets, USP) consists of 84 round, peach tablets containing 0.15 mg of levonorgestrel and 0.03 mg of ethinyl estradiol, and 7 round, white inert tablets. (3)

4 CONTRAINDICATIONS

- A high risk of arterial or venous thrombotic diseases (4)
- Liver tumors or liver disease (4)
- Undiagnosed abnormal uterine bleeding (4)
- Pregnancy (4)
- Breast cancer or other estrogen- or progestin-sensitive cancer (4)
- Use of Hepatitis C drug combinations containing ombitasvir/paritaprevir/ritonavir, with or without dasabuvir, due to the potential for ALT elevations (4)

5 WARNINGS AND PRECAUTIONS

- Thrombotic disorders and other vascular problems: Stop levonorgestrel and ethinyl estradiol if a thrombotic event occurs. Stop at least 4 weeks before and through 2 weeks after major surgery. Start no earlier than 4 weeks after delivery, in women who are not breastfeeding. (5.1)
- Liver disease: Discontinue levonorgestrel and ethinyl estradiol if jaundice occurs. (5.2)
- High blood pressure: If used in women with well-controlled hypertension, monitor blood pressure and stop levonorgestrel and ethinyl estradiol if blood pressure rises significantly. (5.4)
- Carbohydrate and lipid metabolic effects: Monitor prediabetic and diabetic women taking levonorgestrel and ethinyl estradiol. Consider an alternate contraceptive method for women with uncontrolled dyslipidemia. (5.6)
- Headache: Evaluate significant change in headaches and discontinue levonorgestrel and ethinyl estradiol if indicated. (5.7)
- Bleeding irregularities and amenorrhea: Evaluate irregular bleeding or amenorrhea. (5.8)

6 ADVERSE REACTIONS

The most common adverse reactions (≥2%) reported during clinical trials were headache, menorrhagia, nausea, dysmenorrhea, acne, migraine, breast tenderness, weight increased, and depression. (6.1)

To report SUSPECTED ADVERSE REACTIONS, contact Xiromed, LLC at 1-844-XIROMED (1-844-947-6633) or FDA at 1-800-FDA-1088 or www.fda.gov/medwatch.

7 DRUG INTERACTIONS

Drugs or herbal products that induce certain enzymes (for example CYP3A4) may decrease the effectiveness of COCs or increase breakthrough bleeding. Counsel patients to use a back-up or alternative method of contraception when enzyme inducers are used with COCs. (7.1)

8 USE IN SPECIFIC POPULATIONS

- Nursing Mothers: Advise use of another contraceptive method. Levonorgestrel and ethinyl estradiol can decrease milk production. (8.3)

FULL PRESCRIBING INFORMATION

WARNING: CIGARETTE SMOKING AND SERIOUS CARDIOVASCULAR EVENTS

Cigarette smoking increases the risk of serious cardiovascular events from combination oral contraceptive (COC) use. This risk increases with age, particularly in women over 35 years of age, and with the number of cigarettes smoked. For this reason, COCs are contraindicated in women who are over 35 years of age and smoke [see Contraindications (4)].

1 INDICATIONS AND USAGE

Introvale® (levonorgestrel and ethinyl estradiol tablets) is indicated for use by females of reproductive potential to prevent pregnancy.

2 DOSAGE AND ADMINISTRATION

2.1 How to Start Introvale

Introvale is dispensed in an Extended-Cycle Blister Card [see How Supplied/Storage and Handling (16)]. Introvale should be started on a Sunday (see Table 1). For the first cycle of a Sunday Start regimen, an additional method of contraception should be used until after the first 7 consecutive days of administration.

Instruct patients to take Introvale once a day by mouth at the same time every day for 91 days. To achieve maximum contraceptive effectiveness, Introvale should be taken exactly as directed and at intervals not exceeding 24 hours. For patient instructions regarding missed pills, see FDA-approved patient labeling.

2.2 How to Take Introvale

Table 1 Instructions for Administration of Introvale

Starting COCs in women not currently using hormonal contraception (Sunday Start); Important:; Consider the possibility of ovulation and conception prior to initiation of this product.; Tablet Color:; - Introvale active tablets are peach (Day 1 to Day 84). - Introvale inactive tablets are white (Day 85 to Day 91). | Sunday Start:; For each 91-day course, take in the following order:; - Take the first peach tablet (0.15 mg of levonorgestrel and 0.03 mg ethinyl estradiol) on the first Sunday after the onset of menstruation. If menstruation begins on a Sunday, take the tablet on that day. Due to the potential risk of becoming pregnant, use additional non-hormonal contraception (such as condoms or spermicide) for the first 7 days of treatment. - Take subsequent peach tablets once daily at the same time each day for a total of 84 days. - Take one white tablet (inert) daily for the following 7 days and at the same time of day that active tablets were taken. A scheduled period should occur during the 7 days that the white tablets are taken. - Begin the next and all subsequent 91-day courses of Introvale without interruption on the same day of the week (i.e., Sunday) on which the patient began her first dose. Follow the same schedule as the initial 91-day course: a peach tablet once a day for 84 days, and a white tablet once a day for 7 days. If the patient does not immediately start her next pill pack, instruct her to protect herself from pregnancy by using a non-hormonal back-up method of contraception until she has taken a peach tablet daily for 7 consecutive days.
Switching to Introvale from another oral contraceptive | Start on the same day that a new pack of the previous oral contraceptive would have started.
Switching from another contraceptive method to Introvale | Start Introvale:
- Transdermal patch | - On the day when the next application would have been scheduled.
- Vaginal ring | - On the day when the next insertion would have been scheduled.
- Injection | - On the day when the next injection would have been scheduled.
- Intrauterine contraceptive (IUD) | - On the day of removal. - If the IUD is not removed on first day of the patient’s menstrual cycle, additional non- hormonal contraception (such as condoms or spermicide) is needed for the first seven days of the first 91-day course.; days of the first 91-day course.
- Implant | - On the day of removal.
Complete instructions to facilitate patient counseling on proper tablet usage are located in the FDA-approved patient labeling.

Starting Introvale after Abortion or Miscarriage

First-trimester

- After a first-trimester abortion or miscarriage, Introvale may be started immediately. An additional method of contraception is not needed if Introvale is started immediately.
- If Introvale is not started within 5 days after termination of the pregnancy, the patient should use additional non-hormonal contraception (such as condoms or spermicide) for the first seven days of her first 91-day course of Introvale.

Second-trimester

- Do not start until 4 weeks after a second-trimester abortion or miscarriage, due to the increased risk of thromboembolic disease. Start Introvale following the instructions in Table 1 for Sunday start. Use additional non-hormonal contraception (such as condoms or spermicide) for the first seven days of the patient’s first 91-day course of Introvale [see Contraindications (4), Warnings and Precautions (5.1), and FDA-approved Patient Labeling].

Starting Introvale after Childbirth

- Do not start until 4 weeks after delivery, due to the increased risk of thromboembolic disease. Start contraceptive therapy with Introvale following the instructions in Table 1 for women not currently using hormonal contraception.
- Introvale is not recommended for use in lactating women [see Use in Specific Populations (8.3) and FDA-Approved Patient Labeling].
- If the woman has not yet had a period postpartum, consider the possibility of ovulation and conception occurring prior to use of Introvale [see Contraindications (4), Warnings and Precautions (5.1), Use in Specific Populations (8.1 and 8.3), and FDA-approved Patient Labeling].

Tablet Dispenser Instructions:

- The Tablet Dispenser consists of a Tri-Fold Blister Card that holds 91 individually sealed pills (a 13-week, or 91-day, cycle). The 91 pills consist of 84 peach pills (active pills with hormones) and 7 white pills (inactive pills without hormone) arranged in 12 rows of 7 tablets each, labeled weeks “START” through “Week 12” (active pills with hormones) followed by 1 row of 7 white pills, labeled “Week 13” (inactive pills without hormone).

- Advise the patient to remove the first pill in the upper left corner by pushing down on the pill. The pill will come out through a hole in the back of the Tablet Dispenser.
- Advise the patient to wait 24 hours to take the next pill, and continue to take one pill each day until all the pills have been taken.
- Advise the patient, after taking the last white pill, to start taking the first peach pill from a new Tablet Dispenser the very next day, regardless of when their period started.

2.3 Missed Tablets

Table 2 Instructions for Missed Introvale Tablets

- If one active tablet (peach) is missed in Days1 through 84 | Take the tablet as soon as possible. Take the next tablet at the regular time and continue taking one tablet a day until the 91-day course is finished.
- If two consecutive active tablets (peach) are missed in Days 1 through 84 | Take 2 tablets on the day remembered and 2 tablets the next day. Then continue taking one tablet a day until the 91-day course is finished. Additional non-hormonal contraception (such as condoms or spermicide) should be used as back-up if the patient has sex within 7 days after missing 2 tablets.
- If three or more consecutive active tablets (peach) are missed in Days 1 through 84 | Do not take the missed tablets. Continue taking one tablet a day until the 91-day course is finished. Additional non-hormonal contraception (such as condoms or spermicide) must be used as back-up if the patient has sex within 7 days after missing 3 tablets.

2.4 Advice in Case of Gastrointestinal Disturbances

In case of severe vomiting or diarrhea, absorption may not be complete and additional contraceptive measures should be taken. If vomiting or diarrhea occurs within 3 to 4 hours after taking a peach tablet, handle this as a missed tablet [see FDA-approved patient labeling].

3 DOSAGE FORMS AND STRENGTHS

Introvale (levonorgestrel and ethinyl estradiol tablets) are available as round, film-coated, debossed “SZ” on one side, packaged in a unit carton, each containing a 13-week supply of tablets in the following order:

- 84 peach tablets, each containing 0.15 mg of levonorgestrel and 0.03 mg ethinyl estradiol; debossed with “J4” on the other side
- 7 white inert tablets debossed with “J1” on the other side.

4 CONTRAINDICATIONS

Introvale is contraindicated in females who are known to have or develop the following conditions:

- A high risk of arterial or venous thrombotic diseases. Examples include women who are known to:
  - Smoke, if over age 35 [see Boxed Warning and Warnings and Precautions (5.1)].
  - Have deep vein thrombosis or pulmonary embolism, now or in the past [see Warnings and Precautions (5.1)].
  - Have inherited or acquired hypercoagulopathies [see Warnings and Precautions (5.1)].
  - Have cerebrovascular disease [see Warnings and Precautions (5.1)].
  - Have coronary artery disease [see Warnings and Precautions (5.1)].
  - Have thrombogenic valvular or thrombogenic rhythm diseases of the heart (for example, subacute bacterial endocarditis with valvular disease, or atrial fibrillation) [see Warnings and Precautions (5.1)].
  - Have uncontrolled hypertension [see Warnings and Precautions (5.4)].
  - Have diabetes mellitus with vascular disease [see Warnings and Precautions (5.6)].
  - Have headaches with focal neurological symptoms or migraine headaches with aura [see Warnings and Precautions (5.7)].
    - Women over age 35 with any migraine headaches [see Warnings and Precautions (5.7)].
- Liver tumors, benign or malignant, or liver disease [see Warnings and Precautions (5.2) and Use in Specific Populations (8.6)].
- Undiagnosed abnormal uterine bleeding [see Warnings and Precautions (5.8)].
- Pregnancy, because there is no reason to use COCs during pregnancy [see Warnings and Precautions (5.9) and Use in Specific Populations (8.1)].
- Current diagnosis of, or history of, breast cancer, which may be hormone-sensitive [see Warnings and Precautions (5.11)].
- Use of Hepatitis C drug combination containing ombitasvir/paritaprevir/ritonavir, with or without dasabuvir, due to the potential for ALT elevations [see Warnings and Precautions (5.3)]

5 WARNINGS AND PRECAUTIONS

5.1 Thrombotic Disorders and Other Vascular Problems

- Stop levonorgestrel and ethinyl estradiol if an arterial thrombotic event or venous thromboembolic (VTE) event occurs.
- Stop levonorgestrel and ethinyl estradiol if there is unexplained loss of vision, proptosis, diplopia, papilledema, or retinal vascular lesions. Evaluate for retinal vein thrombosis immediately.
- If feasible, stop levonorgestrel and ethinyl estradiol at least 4 weeks before and through 2 weeks after major surgery or other surgeries known to have an elevated risk of VTE as well as during and following prolonged immobilization.
- Start levonorgestrel and ethinyl estradiol no earlier than 4 weeks after delivery, in women who are not breastfeeding. The risk of postpartum VTE decreases after the third postpartum week, whereas the risk of ovulation increases after the third postpartum week.
- The use of COCs increases the risk of VTE. However, pregnancy increases the risk of VTE as much or more than the use of COCs. The risk of VTE in women using COCs is 3 to 9 cases per 10,000 woman- years. The risk of VTE is highest during the first year of use of COCs and when restarting hormonal contraception after a break of 4 weeks or longer. The risk of thromboembolic disease due to COCs gradually disappears after use is discontinued.
- Use of levonorgestrel and ethinyl estradiol provides women with more hormonal exposure on a yearly basis than conventional monthly COCs containing the same strength synthetic estrogens and progestins (an additional 9 weeks of exposure per year). In the clinical trial, one case of pulmonary embolism was reported. Postmarketing adverse reactions of VTE have been reported in women who used levonorgestrel and ethinyl estradiol.
- Use of COCs also increases the risk of arterial thromboses such as strokes and myocardial infarctions, especially in women with other risk factors for these events. Stroke has been reported in women associated with the use of levonorgestrel and ethinyl estradiol. COCs have been shown to increase both the relative and attributable risks of cerebrovascular events (thrombotic and hemorrhagic strokes). This risk increases with age, particularly in women over 35 years of age who smoke.
- Use COCs with caution in women with cardiovascular disease risk factors.

5.2 Liver Disease

Impaired Liver Function

Do not use levonorgestrel and ethinyl estradiol in women with liver disease, such as acute viral hepatitis or severe (decompensated) cirrhosis of the liver [see Contraindications (4)]. Acute or chronic disturbances of liver function may necessitate the discontinuation of COC use until markers of liver function return to normal and COC causation has been excluded. Discontinue levonorgestrel and ethinyl estradiol if jaundice develops.

Liver Tumors

Levonorgestrel and ethinyl estradiol is contraindicated in women with benign and malignant liver tumors [see Contraindications (4)]. Hepatic adenomas are associated with COC use. An estimate of the attributable risk is 3.3 cases/100,000 COC users. Rupture of hepatic adenomas may cause death through intra-abdominal hemorrhage. Studies have shown an increased risk of developing hepatocellular carcinoma in long-term (>8 years) COC users. However, the attributable risk of liver cancers in COC users is less than one case per million users.

5.3 Risk of Liver Enzyme Elevations with Concomitant Hepatitis C Treatment

During clinical trial with the Hepatitis C combination drug regimen that contains ombitasvir/paritaprevir/ritonavir, with or without dasabuvir, ALT elevations greater than 5 times the upper limit of normal (ULN), including some cases greater than 20 times the ULN, were significantly more frequent in women using ethinyl streadiol-containing medications, such as COCs. Discontinue Introvale prior to starting therapy with the combination drug regimen ombitasvir/paritaprevir/ritonavir, with or without dasabuvir. Introvale can be restarted approximately 2 weeks following completion of treatment with Hepatitis C combination drug regimen.

5.4 High Blood Pressure

Levonorgestrel and ethinyl estradiol is contraindicated in women with uncontrolled hypertension or hypertension with vascular disease [see Contraindications (4)]. For women with well-controlled hypertension, monitor blood pressure and stop levonorgestrel and ethinyl estradiol if blood pressure rises significantly.

An increase in blood pressure has been reported in women taking COCs, and this increase is more likely in older women and with extended duration of use. The incidence of hypertension increases with increasing concentration of progestin.

5.5 Gallbladder Disease

Studies suggest a small increased relative risk of developing gallbladder disease among COC users. Use of COCs may worsen existing gallbladder disease.

A past history of COC-related cholestasis predicts an increased risk with subsequent COC use. Women with a history of pregnancy-related cholestasis may be at an increased risk for COC-related cholestasis.

5.6 Carbohydrate and Lipid Metabolic Effects

Carefully monitor prediabetic and diabetic women who are taking levonorgestrel and ethinyl estradiol. COCs may decrease glucose tolerance.

Consider alternative contraception for women with uncontrolled dyslipidemia. A small proportion of women will have adverse lipid changes while on COCs.

Women with hypertriglyceridemia, or a family history thereof, may be at an increased risk of pancreatitis when using COCs.

5.7 Headache

If a woman taking levonorgestrel and ethinyl estradiol develops new headaches that are recurrent, persistent, or severe, evaluate the cause and discontinue levonorgestrel and ethinyl estradiol if indicated.

Consider discontinuation of levonorgestrel and ethinyl estradiol in the case of increased frequency or severity of migraine during COC use (which may be prodromal of a cerebrovascular event) [see Contraindications (4)].

5.8 Bleeding Irregularities and Amenorrhea

Bleeding and/or spotting that occurs at any time while taking the first 84 tablets of each extended-cycle regimen is considered “unscheduled” bleeding/spotting. Bleeding that occurs during the time a woman takes the seven white inert tablets is considered “scheduled” bleeding.

Unscheduled and Scheduled Bleeding and Spotting

Unscheduled (breakthrough) bleeding and spotting sometimes occur in patients on COCs, especially during the first 3 months of use. If unscheduled bleeding persists or occurs after previously regular cycles on levonorgestrel and ethinyl estradiol, check for causes such as pregnancy or malignancy. If pathology and pregnancy are excluded, bleeding irregularities may resolve over time or with a change to a different COC.

Before prescribing levonorgestrel and ethinyl estradiol, advise the woman to weigh the convenience of fewer scheduled menses (4 per year instead of 13 per year) against the inconvenience of increased unscheduled bleeding and/or spotting.

The clinical trial of the efficacy of levonorgestrel and ethinyl estradiol (91-day cycles) in preventing pregnancy also assessed scheduled and unscheduled bleeding. The participants in the study were composed primarily of women who had used oral contraceptives previously as opposed to new users. Women with a history of breakthrough bleeding/spotting ≥ 10 consecutive days on oral contraceptives were excluded from the study. More levonorgestrel and ethinyl estradiol subjects, compared to subjects on the comparator 28-day cycle regimen, discontinued prematurely for unacceptable bleeding (7.7% [levonorgestrel and ethinyl estradiol] vs. 1.8% [28-day cycle regimen]).

Unscheduled bleeding and unscheduled spotting decreased over successive 91-day cycles. Table 3 below presents the number of days with unscheduled bleeding and/or spotting for each respective 91-day cycle.

Table 3 Number of Unscheduled Bleeding and/or Spotting Days per 91-day Cycle

Cycle (N) | Days of Unscheduled Bleeding and/or Spotting per 84-Day Interval |  |  |  | Median Days Per Subject- Month
Cycle (N) | Mean | Q1 | Median | Q3 | Median Days Per Subject- Month
1 (446) | 15.1 | 3 | 12 | 23 | 3
2 (368) | 11.6 | 2 | 6 | 17.5 | 1.5
3 (309) | 10.6 | 1 | 6 | 15 | 1.5
4 (282) | 8.8 | 1 | 4 | 14 | 1

Q1=Quartile 1: 25% of women had ≤ this number of days of unscheduled bleeding/spotting

Median: 50% of women had ≤ this number of days of unscheduled bleeding/spotting

Q3=Quartile 3: 75% of women had ≤ this number of days of unscheduled bleeding/spotting

Table 4 shows the percentages of women with ≥7 days and ≥20 days of unscheduled spotting and/or bleeding in the levonorgestrel and ethinyl estradiol and the 28-day cycle treatment groups.

Table 4 Percentage of Subjects with Unscheduled Bleeding and/or Spotting

Days of unscheduled bleeding and/or spotting | Percentage of Subjectsa
Levonorgestrel and Ethinyl Estradiol | Cycle 1 (N=385) | Cycle 4 (N=261)
≥7 days | 65% | 42%
≥20 days | 35% | 15%
28-day regimen | Cycle 1-4 (N=194) | Cycle 10-13 (N=158)
≥7 days | 38% | 39%
≥20 days | 6% | 4%

aBased on spotting and/or bleeding on days 1 to 84 of a 91 day cycle in the levonorgestrel and ethinyl estradiol subjects and days 1 to 21 of a 28 day cycle over 4 cycles in the 28-day dosing regimen.

Total days of bleeding and/or spotting (scheduled plus unscheduled) were similar over one year of treatment for levonorgestrel and ethinyl estradiol subjects and subjects on the 28-day cycle regimen.

Amenorrhea and Oligomenorrhea

Women who are not pregnant and use levonorgestrel and ethinyl estradiol may experience amenorrhea. Based on data from the clinical trial, amenorrhea occurred in approximately 0.8% of women during Cycle 1, 1.2% of women during Cycle 2, 3.7% of women during Cycle 3, and 3.4% of women during Cycle 4. Because women using levonorgestrel and ethinyl estradiol will likely have scheduled bleeding only 4 times per year, rule out pregnancy at the time of any missed menstrual period.

Some women may experience amenorrhea or oligomenorrhea after stopping COCs, especially when such a condition was pre-existent.

5.9 COC Use Before or During Early Pregnancy

Extensive epidemiological studies have revealed no increased risk of birth defects in women who have used oral contraceptives prior to pregnancy. Studies also do not suggest a teratogenic effect, particularly in so far as cardiac anomalies and limb-reduction defects are concerned, when oral contraceptives are taken inadvertently during early pregnancy. Discontinue levonorgestrel and ethinyl estradiol use if pregnancy is confirmed.

Administration of oral contraceptives to induce withdrawal bleeding should not be used as a test for pregnancy [see Use in Specific Populations (8.1)].

5.10 Depression

Depression associated with the use of levonorgestrel and ethinyl estradiol has been reported. Carefully observe women with a history of depression and discontinue levonorgestrel and ethinyl estradiol if severe depression recurs.

5.11 Malignant Neoplasms

Breast Cancer
Introvale is contraindicated in females who currently have or have had breast cancer because breast cancer may be hormonally sensitive [see Contraindications (4)].
Epidemiology studies have not found a consistent association between use of combined oral contraceptives (COCs) and breast cancer risk. Studies do not show an association between ever (current or past) use of COCs and risk of breast cancer. However, some studies report a small increase in the risk of breast cancer among current or recent users (<6 months since last use) and current users with longer duration of COC use [see Postmarketing Experience (6.2)].
Cervical Cancer

Some studies suggest that COC use has been associated with an increase in the risk of cervical cancer or intraepithelial neoplasia. However, there continues to be controversy about the extent to which such findings may be due to differences in sexual behavior and other factors.

5.12 Effect on Binding Globulins

The estrogen component of COCs may raise the serum concentrations of thyroxine-binding globulin, sex hormone-binding globulin and cortisol-binding globulin. The dose of replacement thyroid hormone or cortisol therapy may need to be increased.

5.13 Monitoring

A woman who is taking COCs should have a yearly visit with her healthcare provider for a blood pressure check and for other indicated health care.

5.14 Hereditary Angioedema

In women with hereditary angioedema, exogenous estrogens may induce or exacerbate symptoms of angioedema.

5.15 Chloasma

Chloasma may occasionally occur, especially in women with a history of chloasma gravidarum. Women with a tendency to develop chloasma should avoid prolonged exposure to the sun or ultraviolet radiation while taking levonorgestrel and ethinyl estradiol.

6 ADVERSE REACTIONS

The following serious adverse reactions with the use of COCs are discussed elsewhere in the labeling:

- Serious cardiovascular events and stroke [see Boxed Warning and Warnings and Precautions (5.1)]
- Vascular events [see Warnings and Precautions (5.1)]
- Liver disease [see Warnings and Precautions (5.2)]

Adverse reactions commonly reported by COC users are:

- Irregular uterine bleeding
- Nausea
- Breast tenderness
- Headache

6.1 Clinical Trial Experience

Because clinical trials are conducted under widely varying conditions, adverse reaction rates observed in the clinical trials of a drug cannot be directly compared to the rates in the clinical trials of another drug and may not reflect the rates observed in clinical practice.

The clinical trial that evaluated the safety and efficacy of levonorgestrel and ethinyl estradiol was a 12-month, randomized, multicenter, open-label study, which enrolled women aged 18 to 40, of whom 456 took at least one dose of levonorgestrel and ethinyl estradiol (345.14 woman-years of exposure) [see Clinical Studies (14)].

Adverse Reactions Leading to Study Discontinuation: 14.9% of the women discontinued from the clinical trial due to an adverse reaction; the most common adverse reactions (≥1% of women) leading to discontinuation in the levonorgestrel and ethinyl estradiol group were menorrhagia (5.7%), mood swings (1.9%), weight/appetite increase (1.5%), and acne (1.3%).

Common Adverse Reactions (≥2% of women): headache (20.6%), menorrhagia (11.6%), nausea (7.5%), dysmenorrhea (5.7%), acne (4.6%), migraine (4.4%), breast tenderness (3.5%), weight increased (3.1%), and depression (2.1%).

Serious Adverse Reactions: pulmonary embolus, cholecystitis.

6.2 Postmarketing Experience

Five studies that compared breast cancer risk between ever-users (current or past use) of COCs and never-users of COCs reported no association between ever use of COCs and breast cancer risk, with effect estimates ranging from 0.90 - 1.12 (Figure A).
Three studies compared breast cancer risk between current or recent COC users (<6 months since last use) and never users of COCs (Figure A). One of these studies reported no association between breast cancer risk and COC use. The other two studies found an increased relative risk of 1.19 - 1.33 with current or recent use. Both of these studies found an increased risk of breast cancer with current use of longer duration, with relative risks ranging from 1.03 with less than one year of COC use to approximately 1.4 with more than 8-10 years of COC use.
Figure A: Relevant Studies of Risk of Breast Cancer with Combined Oral Contraceptives

RR = relative risk; OR = odds ratio; HR = hazard ratio. “ever COC” are females with current or past COC use; “never COC use” are females that never used COCs.

The following adverse reactions have been identified during post-approval use of levonorgestrel and ethinyl estradiol. Because these reactions are reported voluntarily from a population of uncertain size, it is not possible to reliably estimate their frequency or establish a causal relationship to drug exposure.

Gastrointestinal disorders: abdominal distension, vomiting

General disorders and administration site conditions: chest pain, fatigue, malaise, edema peripheral, pain

Immune system disorder: hypersensitivity reactions, including itching, rash, and angioedema

Investigations: blood pressure increased

Musculoskeletal and connective tissue disorders: muscle spasms, pain in extremity

Nervous system disorders: dizziness, loss of consciousness

Psychiatric disorders: insomnia

Reproductive and breast disorders: dysmenorrhea

Skin and subcutaneous tissue disorders: alopecia

Vascular disorders: thrombosis, pulmonary embolism, pulmonary thrombosis

7 DRUG INTERACTIONS

Consult the labeling of concurrently used drugs to obtain further information about interactions with hormonal contraceptives or the potential for enzyme alterations.

7.1 Effects of Other Drugs on Combined Oral Contraceptives

Substances decreasing the plasma concentrations of COCs and potentially diminishing the efficacy of COCs

Drugs or herbal products that induce certain enzymes, including cytochrome P450 3A4 (CYP3A4), may decrease the plasma concentrations of COCs and potentially diminish the effectiveness of COCs or increase breakthrough bleeding. Some drugs or herbal products that may decrease the effectiveness of hormonal contraceptives include phenytoin, barbiturates, carbamazepine, bosentan, felbamate, griseofulvin, oxcarbazepine, rifampicin, topiramate, rifabutin, rufinamide, aprepitant, and products containing St. John’s wort. Interactions between oral contraceptives and other drugs may lead to breakthrough bleeding and/or contraceptive failure. Counsel women to use an alternative method of contraception or a back-up method when enzyme inducers are used with COCs, and to continue back-up contraception for 28 days after discontinuing the enzyme inducer to ensure contraceptive reliability.

Colesevelam

Colesevelam, a bile acid sequestrant, given together with a COC, has been shown to significantly decrease the AUC of EE. The drug interaction between the contraceptive and colesevelam was decreased when the two drug products were given 4 hours apart.

Substances increasing the plasma concentrations of COCs

Co-administration of atorvastatin or rosuvastatin and certain COCs containing ethinyl estradiol (EE) increase AUC values for EE by approximately 20 to 25%. Ascorbic acid and acetaminophen may increase plasma EE concentrations, possibly by inhibition of conjugation. CYP3A4 inhibitors such as itraconazole, voriconazole, fluconazole, grapefruit juice, or ketoconazole may increase plasma hormone concentrations.

Human immunodeficiency virus (HIV)/ Hepatitis C virus (HCV) protease inhibitors and non-nucleoside reverse transcriptase inhibitors

Significant changes (increase or decrease) in the plasma concentrations of estrogen and/or progestin have been noted in some cases of co-administration with HIV protease inhibitors (decrease [e.g., nelfinavir, ritonavir, darunavir/ritonavir, (fos)amprenavir/ritonavir, lopinavir/ritonavir, and tipranavir/ritonavir] or increase [e.g., indinavir and atazanavir/ritonavir])/HCV protease inhibitors (decrease [e.g., nevirapine] or increase [e.g., etravirine]).

7.2 Effects of Combined Oral Contraceptives on Other Drugs

COCs containing EE may inhibit the metabolism of other compounds (e.g., cyclosporine, prednisolone, theophylline, tizanidine, and voriconazole) and increase their plasma concentrations.

COCs have been shown to decrease plasma concentrations of acetaminophen, clofibric acid, morphine, salicylic acid, temazepam and lamotrigine. Significant decrease in plasma concentration of lamotrigine has been shown, likely due to induction of lamotrigine glucuronidation. This may reduce seizure control; therefore, dosage adjustments of lamotrigine may be necessary.

Women on thyroid hormone replacement therapy may need increased doses of thyroid hormone because the serum concentration of thyroid-binding globulin increases with use of COCs [see Warnings and Precautions (5.12)].

7.3 Concomitant Use with Hepatitis C Vaccine (HCV) Combination Therapy - Liver Enzyme Elevation

Do not administer Introvale with HCV drug combinations containing ombitasvir/paritaprevir/ritonavir, with or without dasabuvir, due to potential for ALT elevations.

7.4 Interactions with Laboratory Tests

The use of contraceptive steroids may influence the results of certain laboratory tests, such as coagulation factors, lipids, glucose tolerance, and binding proteins.

8 USE IN SPECIFIC POPULATIONS

8.1 Pregnancy

There is little or no increased risk of birth defects in women who inadvertently use COCs during early pregnancy. Epidemiologic studies and meta-analyses have not found an increased risk of genital or non-genital birth defects (including cardiac anomalies and limb-reduction defects) following exposure to low dose COCs prior to conception or during early pregnancy.

Do not administer COCs to induce withdrawal bleeding as a test for pregnancy. Do not use COCs during pregnancy to treat threatened or habitual abortion.

8.3 Nursing Mothers

Advise the nursing mother to use other forms of contraception, when possible, until she has weaned her child. COCs can reduce milk production in breastfeeding mothers. This is less likely to occur once breastfeeding is well established; however, it can occur at any time in some women. Small amounts of oral contraceptive steroids and/or metabolites are present in breast milk.

8.4 Pediatric Use

Safety and efficacy of levonorgestrel and ethinyl estradiol have been established in women of reproductive age. Efficacy is expected to be the same for postpubertal adolescents under the age of 18 as for users 18 years and older. Use of levonorgestrel and ethinyl estradiol before menarche is not indicated.

8.5 Geriatric Use

Levonorgestrel and ethinyl estradiol has not been studied in postmenopausal women and is not indicated in this population.

8.6 Hepatic Impairment

The pharmacokinetics of levonorgestrel and ethinyl estradiol have not been studied in subjects with hepatic impairment. However, steroid hormones may be poorly metabolized in patients with hepatic impairment. Acute or chronic disturbances of liver function may necessitate the discontinuation of COC use until markers of liver function return to normal and COC causation has been excluded [see Contraindications (4) and Warnings and Precautions (5.2)].

8.7 Renal Impairment

The pharmacokinetics of levonorgestrel and ethinyl estradiol have not been studied in women with renal impairment.

10 OVERDOSAGE

There have been no reports of serious ill effects from overdose of oral contraceptives, including ingestion by children. Overdosage may cause withdrawal bleeding in females and nausea.

11 DESCRIPTION

Introvale (levonorgestrel and ethinyl estradiol tablets) is an extended-cycle combination oral contraceptive consisting of 84 peach active tablets each containing 0.15 mg of levonorgestrel, a synthetic progestin and 0.03 mg of ethinyl estradiol, an estrogen, and 7 white inert tablets (without hormones).

The structural formulas for the active components are:

Levonorgestrel C21H28O2 MW:312.4

Levonorgestrel is chemically 18,19-Dinorpregn-4-en-20-yn-3-one, 13-ethyl-17-hydroxy-, (17α)-, (-)-.

Ethinyl Estradiol C20H24O2 MW:296.4

Ethinyl Estradiol is 19-Norpregna-1,3,5(10)-trien-20-yne-3,17-diol, (17α)-.

- Each peach active tablet contains the following inactive ingredients: lactose anhydrous, magnesium stearate, povidone, polyvinyl alcohol, polyethylene glycol, titanium dioxide, talc, iron oxide yellow, iron oxide red and iron oxide black.
- Each white inert tablet contains the following inactive ingredients: lactose anhydrous, magnesium stearate, povidone, polyvinyl alcohol, polyethylene glycol, talc and titanium dioxide.

12 CLINICAL PHARMACOLOGY

12.1 Mechanism of Action

COCs lower the risk of becoming pregnant primarily by suppressing ovulation. Other possible mechanisms may include cervical mucus changes that inhibit sperm penetration and endometrial changes that reduce the likelihood of implantation.

12.2 Pharmacodynamics

No specific pharmacodynamic studies were conducted with levonorgestrel and ethinyl estradiol.

12.3 Pharmacokinetics

Absorption

No specific investigation of the absolute bioavailability of levonorgestrel and ethinyl estradiol in humans has been conducted. However, literature indicates that levonorgestrel is rapidly and completely absorbed after oral administration (bioavailability nearly 100%) and is not subject to first-pass metabolism. EE is rapidly and almost completely absorbed from the gastrointestinal tract but, due to first-pass metabolism in gut mucosa and liver, the bioavailability of EE is approximately 43%.

Following continuous dosing with once-daily administration of levonorgestrel and ethinyl estradiol tablets, plasma concentrations of levonorgestrel and EE reached steady-state within 7 days. The mean plasma pharmacokinetic parameters for levonorgestrel and ethinyl estradiol under fasting conditions in normal healthy women following once-daily administration of one levonorgestrel/EE combination tablet for 10 days are summarized in Table 5.

Table 5 Mean ±SD Pharmacokinetic Parameters Under Fasting Conditions in Healthy Women Following 10 Days Administration of One Tablet of Levonorgestrel and Ethinyl Estradiol (n=44)

Analyte | AUC0-24 | Cmax | Cmin | Cavga | Tmax
Levonorgestrel | 54.6 ± 16.5; ng*hr/mL | 5 ± 1.5 ng/mL | 1.6 ± 0.5; ng/mL | 2.3 ± 0.7; ng/mL | 1.4 ± 0.7 hours
Ethinyl Estradiol | 935.5 ± 346.9; pg*hr/mL | 106.1 ± 41.2; pg/mL | 18.5±9.4; pg/mL | 38.9 ± 14.4; pg/mL | 1.6 ± 0.6; hours

aCavg = AUC0-24/24

Food Effect

The effect of food on the rate and the extent of levonorgestrel and EE absorption following oral administration of levonorgestrel and ethinyl estradiol has not been evaluated.

Distribution

The apparent volume of distribution of levonorgestrel and EE are reported to be approximately 1.8 L/kg and 4.3 L/kg, respectively. Levonorgestrel is about 97.5 to 99% protein-bound, principally to sex hormone binding globulin (SHBG) and, to a lesser extent, serum albumin. EE is about 95 to 97% bound to serum albumin. EE does not bind to SHBG, but induces SHBG synthesis, which leads to decreased levonorgestrel clearance. Following repeated daily dosing of levonorgestrel/EE oral contraceptives, levonorgestrel plasma concentrations accumulate more than predicted based on single-dose pharmacokinetics, due in part, to increased SHBG levels that are induced by EE, and a possible reduction in hepatic metabolic capacity.

Metabolism

Following absorption, levonorgestrel is conjugated at the 17β-OH position to form sulfate and to a lesser extent, glucuronide conjugates in plasma. Significant amounts of conjugated and unconjugated 3α,5β-tetrahydrolevonorgestrel are also present in plasma, along with much smaller amounts of 3α,5α-tetrahydrolevonorgestrel and 16β-hydroxylevonorgestrel. Levonorgestrel and its phase I metabolites are excreted primarily as glucuronide conjugates. Metabolic clearance rates may differ among individuals by several-fold, and this may account in part for the wide variation observed in levonorgestrel concentrations among users.

First-pass metabolism of EE involves formation of EE-3-sulfate in the gut wall, followed by 2-hydroxylation of a portion of the remaining untransformed EE by hepatic cytochrome P-450 3A4 (CYP3A4). Levels of CYP3A4 vary widely among individuals and can explain the variation in rates of EE hydroxylation. Hydroxylation at the 4-, 6-, and 16- positions may also occur, although to a much lesser extent than 2-hydroxylation. The various hydroxylated metabolites are subject to further methylation and/or conjugation.

Excretion

About 45% of levonorgestrel and its metabolites are excreted in the urine and about 32% are excreted in feces, mostly as glucuronide conjugates. The terminal elimination half-life for levonorgestrel after a single dose of levonorgestrel and ethinyl estradiol was about 30 hours.

EE is excreted in the urine and feces as glucuronide and sulfate conjugates, and it undergoes enterohepatic recirculation. The terminal elimination half-life of EE after a single dose of levonorgestrel and ethinyl estradiol was found to be about 15 hours.

13 NONCLINICAL TOXICOLOGY

13.1 Carcinogenesis, Mutagenesis, Impairment of Fertility

[see Warnings and Precautions (5.2, 5.10) and Use in Specific Populations (8.1)].

14 CLINICAL STUDIES

In a 12-month, multicenter, randomized, open-label clinical trial, 456 women aged 18 to 40 were studied to assess the safety and efficacy of levonorgestrel and ethinyl estradiol, completing 809 91-day cycles of exposure. The racial demographic of those enrolled was: Caucasian (77%), African-American (11%), Hispanic (7%), Asian (2%), and Other (3%).

There were no exclusions for body mass index (BMI) or weight. The weight range of those women treated was 84 to 304 pounds, with a mean weight of 157 pounds and a median weight of 147 pounds. Among the women in the trial, 63% were current or recent hormonal contraceptive users, 29% were prior users (who had used hormonal contraceptives in the past but not in the 6 months prior to enrollment), and 8% were new starts.

The pregnancy rate (Pearl Index [PI]) in the 397 women aged 18 to 35 years was 1.98 pregnancies per 100 women-years of use (95% CI: 0.54 to 5.03), based on 4 pregnancies that occurred after the onset of treatment and within 14 days after the last combination pill. Cycles in which conception did not occur, but which included the use of back-up contraception, were not included in the calculation of the PI.

16 HOW SUPPLIED/STORAGE AND HANDLING

16.1 How Supplied

Introvale tablets (levonorgestrel and ethinyl estradiol, USP) are available in extended-cycle blister cards (NDC 70700-117-87), each containing a 13-week supply of tablets: 84 peach active tablets, each containing 0.15 mg of levonorgestrel and 0.03 mg ethinyl estradiol, and 7 white inert tablets packaged in a unit carton. The active tablets are peach, round, film-coated, debossed “SZ” on one side and “J4” on the other side. The inert tablets are white, round, film-coated, debossed with “SZ” on one side and “J1” on the other side.

16.2 Storage Conditions

- Store at 20° to 25° C (68° to 77° F) [see USP Controlled Room Temperature].
- Protect from light.

17 PATIENT COUNSELING INFORMATION

See FDA-approved patient labeling (Patient Information and Instructions for Use).

Counsel patients on the following information:

- Cigarette smoking increases the risk of serious cardiovascular events from COC use, and that women who are over 35 years old and smoke should not use COCs [see Boxed Warning].
- Increased risk of VTE compared to non-users of COCs is greatest after initially starting a COC or restarting (following a 4-week or greater pill-free interval) the same or a different COC [see Warnings and Precautions (5.1)].
- Introvale does not protect against HIV-infection (AIDS) and other sexually transmitted infections.
- Introvale is not to be used during pregnancy; if pregnancy occurs during use of Introvale, instruct the patient to stop further use [see Warnings and Precautions (5.8)].
- Take one tablet daily by mouth at the same time every day. Instruct patients what to do in the event tablets are missed [see Dosage and Administration (2.3)].
- Use a back-up or alternative method of contraception when enzyme inducers are used with Introvale [see Drug Interactions (7.1)].
- COCs may reduce breast milk production; this is less likely to occur if breastfeeding is well established [see Use in Specific Populations (8.3)].
- Women who start on COCs postpartum, and who have not yet had a period, should use an additional method of contraception until they have taken a peach tablet for 7 consecutive days [see Dosage and Administration (2.2)].
- Amenorrhea may occur. Because women using Introvale will likely have scheduled bleeding only 4 times per year, rule out pregnancy at the time of any missed menstrual period [see Warnings and Precautions (5.7)].

INTROVALE is a registered trademark of Xiromed Pharma España, S.L.

Manufactured by Laboratorios Leon Farma S.A., Spain

For Xiromed LLC, Florham Park NJ 07932

Product of Spain

Rev. 06/2022
PI-117-03

PATIENT INFORMATION

Introvale®

Levonorgestrel and Ethinyl Estradiol Tablets, USP

0.15 mg/0.03 mg

(lee-voe-nor-JES-trel ETH-in-il es-tra-DIE-ole)

What is the most important information I should know about Introvale?

Do not use Introvale if you smoke cigarettes and are over 35 years old. Smoking increases your risk of serious cardiovascular side effects from hormonal birth control pills, including death from heart attack, blood clots or stroke. This risk increases with age and the number of cigarettes you smoke.

What is Introvale?

Introvale is a birth control pill (oral contraceptive) used by women to prevent pregnancy.

How does Introvale work for contraception?

Your chance of getting pregnant depends on how well you follow the directions for taking your birth control pills. The better you follow the directions, the less chance you have of getting pregnant.

Based on the results of clinical studies, about 1 to 5 out of 100 women may get pregnant during the first year they use Introvale.

The following chart shows the chance of getting pregnant for women who use different methods of birth control. Each box on the chart contains a list of birth control methods that are similar in effectiveness. The most effective methods are at the top of the chart. The box on the bottom of the chart shows the chance of getting pregnant for women who do not use birth control and are trying to get pregnant.

Who should not take Introvale?

Do not take Introvale if you:

- smoke and are over 35 years of age
- had blood clots in your arms, legs, lungs, or eyes
- had a problem with your blood that makes it clot more than normal
- have certain heart valve problems or irregular heart beat
- had a stroke
- had a heart attack
- have high blood pressure that cannot be controlled by medicine
- have diabetes with kidney, eye, nerve, or blood vessel damage
- have certain kinds of severe migraine headaches with aura, numbness, weakness or changes in vision, or any migraine headaches if you are over 35 years of age
- have liver problems, including liver tumors
- take any Hepatitis C drug combination containing ombitasvir/paritaprevir/ritonavir, with or without dasabuvir. This may increase levels of the liver enzyme "alanine aminotransferase" (ALT) in the blood.
- have any unexplained vaginal bleeding
- are pregnant
- had breast cancer or any cancer that is sensitive to female hormones

If any of these conditions happen while you are taking Introvale, stop taking Introvale right away and talk to your healthcare provider. Use non-hormonal contraception when you stop taking Introvale.

What should I tell my healthcare provider before taking Introvale?

Tell your healthcare provider if you:

- are pregnant or think you may be pregnant
- are depressed now or have been depressed in the past
- had yellowing of your skin or eyes (jaundice) caused by pregnancy (cholestasis of pregnancy)
- are breastfeeding or plan to breastfeed. Introvale may decrease the amount of breast milk you make. A small amount of the hormones in levonorgestrel and ethinyl estradiol may pass into your breast milk. Talk to your healthcare provider about the best birth control method for you while breastfeeding.

Tell your healthcare provider about all the medicines you take, including prescription and over-the-counter medicines, vitamins and herbal supplements.

Introvale may affect the way other medicines work, and other medicines may affect how well Introvale works.

Know the medicines you take. Keep a list of them to show your healthcare provider and pharmacist when you get a new medicine.

How should I take Introvale?

Read the Instructions for Use at the end of this Patient Information.

What are the possible serious side effects of Introvale?

- Like pregnancy, Introvale may cause serious side effects, including blood clots in your lungs, heart attack, or a stroke that may lead to death. Some other examples of serious blood clots include blood clots in the legs or eyes.

Serious blood clots can happen especially if you smoke, are obese, or are older than 35 years of age. Serious blood clots are more likely to happen when you:

o first start taking birth control pills

o restart the same or different birth control pills after not using them for a month or more

Call your healthcare provider or go to a hospital emergency room right away if you have:

o leg pain that will not go away
o sudden severe shortness of breath
o sudden change in vision or blindness
o chest pain
o a sudden, severe headache unlike your usual headaches
o weakness or numbness in your arm or leg
o trouble speaking

Other serious side effects include:

- liver problems, including:
  - rare liver tumors
  - jaundice (cholestasis), especially if you previously had cholestasis of pregnancy. Call your healthcare provider if you have yellowing of your skin or eyes.
- high blood pressure. You should see your healthcare provider for a yearly check of your blood pressure.
- gallbladder problems
- changes in the sugar and fat (cholesterol and triglycerides) levels in your blood
- new or worsening headaches including migraine headaches
- irregular or unusual vaginal bleeding and spotting between your menstrual periods, especially during the first 3 months of taking Introvale.
- Depression
- possible cancer in your breast and cervix
- swelling of your skin especially around your mouth, eyes, and in your throat (angioedema). Call your healthcare provider if you have a swollen face, lips, mouth tongue or throat, which may lead to difficulty swallowing or breathing. Your chance of having angioedema is higher if you have a history of angioedema.
- dark patches of skin around your forehead, nose, cheeks and around your mouth, especially during pregnancy (chloasma).Women who tend to get chloasma should avoid spending a long time in sunlight, tanning booths, and under sun lamps while taking Introvale. Use sunscreen if you have to be in the sunlight.

What are the most common side effects of Introvale?

- headache (migraine)
- heavier or longer periods, pain with periods
- nausea
- acne
- breast tenderness
- increase in weight

These are not all the possible side effects of Introvale. For more information, ask your healthcare provider or pharmacist.

You may report side effects to the FDA at 1-800-FDA-1088.

What else should I know about taking Introvale?

- If you are scheduled for any lab tests, tell your healthcare provider you are taking Introvale. Certain blood tests may be affected by Introvale.
- Introvale does not protect against HIV infection (AIDS) and other sexually transmitted infections.

How should I store Introvale?

Store Introvale at room temperature between 68°F to 77°F (20°C to 25°C).

- Protect from light.

General information about the safe and effective use of Introvale.

Medicines are sometimes prescribed for purposes other than those listed in a Patient Information leaflet. Do not use Introvale for a condition for which it was not prescribed. Do not give Introvale to other people, even if they have the same symptoms that you have.

This Patient Information summarizes the most important information about Introvale. You can ask your pharmacist or healthcare provider for information about Introvale that is written for health professionals.

For more information, call Xiromed, LLC. at 1-844-XIROMED (844-947-6633).

Do birth control pills cause cancer?

It is not known if hormonal birth control pills cause breast cancer. Some studies, but not all, suggest that there could be a slight increase in the risk of breast cancer among current users with longer duration of use.
If you have breast cancer now, or have had it in the past, do not use hormonal birth control because some breast cancers are sensitive to hormones.

Women who use birth control pills may have a slightly higher chance of getting cervical cancer. However, this may be due to other reasons such as having more sexual partners.

What if I want to become pregnant?

You may stop taking the pill whenever you wish. Consider a visit with your healthcare provider for a pre-pregnancy checkup before you stop taking the pill.

What should I know about my period when taking Introvale?

When you take Introvale, which has a 91-day extended dosing cycle, you should have 4 scheduled periods a year (bleeding when you are taking the 7 white pills). However, you will probably have more bleeding or spotting between your scheduled periods than if you were using a birth control pill with a 28-day dosing cycle. During the first Introvale 91-day treatment cycle, about 1 in 3 women may have 20 or more days of unplanned bleeding or spotting. This bleeding or spotting tends to decrease with time. Do not stop taking Introvale because of this bleeding or spotting. If the spotting continues for more than 7 days in a row or if the bleeding is heavy, call your healthcare provider.

What are the ingredients in Introvale?

Active ingredients: Each peach pill contains levonorgestrel and ethinyl estradiol.

Inactive ingredients:

Peach pills: lactose anhydrous, magnesium stearate, povidone, polyvinyl alcohol, polyethylene glycol, titanium dioxide, talc, iron oxide yellow, iron oxide red and iron oxide black.

White pills: lactose anhydrous, magnesium stearate, povidone, polyvinyl alcohol, polyethylene glycol, talc and titanium dioxide.

Instructions For Use

Introvale

(levonorgestrel and ethinyl estradiol tablets, USP)

(lee-voe-nor-JES-trel ETH-in-il es-tra-DIE-ole)

Important Information about taking Introvale

- Take 1 pill every day at the same time. Take the pills in the order directed on your pill dispenser.
- Do not skip your pills, even if you do not have sex often. If you miss pills (including starting the pack late) you could get pregnant. The more pills you miss, the more likely you are to get pregnant.
- If you have trouble remembering to take Introvale, talk to your healthcare provider.
- When you first start taking Introvale, spotting or light bleeding in between your periods may occur. Contact your healthcare provider if this does not go away after a few months.
- You may feel sick to your stomach (nauseous), especially during the first few months of taking Introvale. If you feel sick to your stomach, do not stop taking the pill. The problem will usually go away. If your nausea does not go away, call your healthcare provider.
- Missing pills can also cause spotting or light bleeding, even when you take the missed pills later. On the days you take 2 pills to make up for missed pills (see What should I do if I miss any Introvale pills? below), you could also feel a little sick to your stomach.
- It is not uncommon to miss a period. However, if you miss a period and have not taken Introvale according to directions, or feel like you may be pregnant, call your healthcare provider. If you have a positive pregnancy test, you should stop taking Introvale.
- If you have vomiting or diarrhea within 3 to 4 hours of taking a peach pill, take another peach pill as soon as possible. Continue taking one pill a day until the 91-day course is finished.
- If you have vomiting or diarrhea for more than 1 day, your birth control pills may not work as well. Use an additional birth control method, like condoms or spermicide, until you check with your healthcare provider.
- Stop taking Introvale at least 4 weeks before you have major surgery and do not restart after the surgery without asking your healthcare provider. Be sure to use other forms of contraception (like condoms or spermicide) during this time period.

Before you start taking Introvale:

- Decide what time of day you want to take your pill. It is important to take it at about the same time every day.
- Look at your Extended-Cycle Blister Cards. Your Tablet Dispenser consists of a Tri-Fold Blister Card that holds 91 individually sealed pills (a 13-week, or 91-day, cycle). The 91 pills consist of 84 peach pills (active pills with hormones) and 7 white pills (inactive pills without hormone) arranged in 12 rows of 7 tablets each, labeled weeks “START” through “Week 12” (active pills with hormones) followed by 1 row of 7 white pills, labeled “Week 13” (inactive pills without hormone).

- Also find:

o Where on the first tray in the pack to start taking pills (upper left corner) and
o In what order to take the pills (follow the weeks)

- Be sure you have ready at all times another kind of birth control (such as condoms or spermicide), to use as a back-up in case you miss pills.

When should I start taking Introvale?

If you start taking Introvale and you have not used a hormonal birth control method before:

- Take the first peach pill on the Sunday after your period starts, even if you are still bleeding. If your period begins on Sunday, start the first peach pill that same day.
- Use another method of birth control (such as condoms or spermicides) as a back-up method if you have sex anytime from the Sunday you start your first peach pill until the next Sunday (first 7 days).

If you start taking Introvale and you are switching from another birth control pill:

- Start your new Introvale pack on the same day that you would start the next pack of your previous birth control method.
- Do not continue taking the pills from your previous birth control pack.

If you start taking Introvale and previously used a vaginal ring:

- Start using Introvale on the day you would have reapplied the next ring.

If you start taking Introvale and previously used a transdermal patch:

- Start using Introvale on the day you would have started a new cycle (first patch application).

If you start taking Introvale and you are switching from a progestin-only method such as an implant or injection:

- Start taking Introvale on the day of removal of your implant, or on the day when you would have had your next injection.

If you start taking Introvale and you are switching from an intrauterine device or system (IUD or IUS):

- Start taking Introvale on the day of removal of your IUD or IUS.
- You do not need back-up contraception if your IUD or IUS is removed on the first day (Day 1) of your period. If your IUD or IUS is removed on any other day, use non-hormonal back-up contraception such as condoms or spermicide for the first 7 days that you take Introvale.

Keep a calendar to track your period: If this is the first time you are taking birth control pills, read, “When should I start taking Introvale ?” above. Follow these instructions for a Sunday Start.

Instructions for using your Introvale Extended-Cycle Blister Cards:

Sunday Start:

Take pill 1 on the Sunday after your period starts. To remove your pill from the dispenser, press the pill through the hole in the bottom of the dispenser. See Figure C.

Figure C

- If your period starts on a Sunday, take pill “1” that same day.
- Take 1 pill at about the same time every day until you have taken the last pill in the tablet dispenser.
- After taking the last white pill on Day 91 from the pill dispenser, start taking the first peach pill from a new Extended-Cycle blister card on the very next day (this should be a Sunday). Take the first pill in the new pack whether or not you are having your period.
- Use non-hormonal back-up contraception such as condoms or spermicide for the first 7 days of the first cycle that you take Introvale.

What should I do if I miss any Introvale pills?

If you miss 1 peach pill, follow these steps:

- Take it as soon as you remember. Take the next pill at your regular time.

This means you may take 2 pills in 1 day.

- Then continue taking 1 pill every day until you finish the pack.
- You do not need to use a back-up birth control method if you have sex.

If you miss 2 peach pills in a row, follow these steps:

- Take 2 pills on the day you remember and 2 pills the next day.
- Then continue to take 1 pill every day until you finish the pack.
- You could become pregnant if you have sex in the 7 days after you miss two pills. You must use a non-hormonal birth control method (such as a condom or spermicide) as a back-up if you have sex during the first 7 days after you restart your pills.

If you miss 3 or more peach pills in a row, follow these steps:

- Do not take the missed pills. Keep taking 1 pill every day until you have completed all of the remaining pills in the pack. For example, if you start taking the pill on Thursday, take the pill under “Thursday” and do not take the missed pills. You may have bleeding during the week following the missed pills.
- You could become pregnant if you have sex during the days of missed pills or during the first 7 days after restarting your pills. You must use a non-hormonal birth control method (such as a condom or spermicide) as a back-up when you miss pills and for the first 7 days after you restart your pills. If you do not have your period when you are taking the white pills, call your healthcare provider because you may be pregnant.

If you have any questions or are unsure about the information in this leaflet, call your healthcare provider.

This Patient Information and Instructions for Use have been approved by the U.S. Food and Drug Administration.

INTROVALE is a registered trademark of Xiromed Pharma España, S.L.

Manufactured by Laboratorios Leon Farma S.A., Spain

For Xiromed LLC, Florham Park NJ 07932

Product of Spain

Rev: 06/2022
PIL-117-03

PACKAGE LABEL.PRINCIPAL DISPLAY PANEL

Introvale (Levonorgestrel and Ethinyl Estradiol Tablets, USP) 0.15 mg/0.03 mg - NDC 70700-117-87 - Carton Label